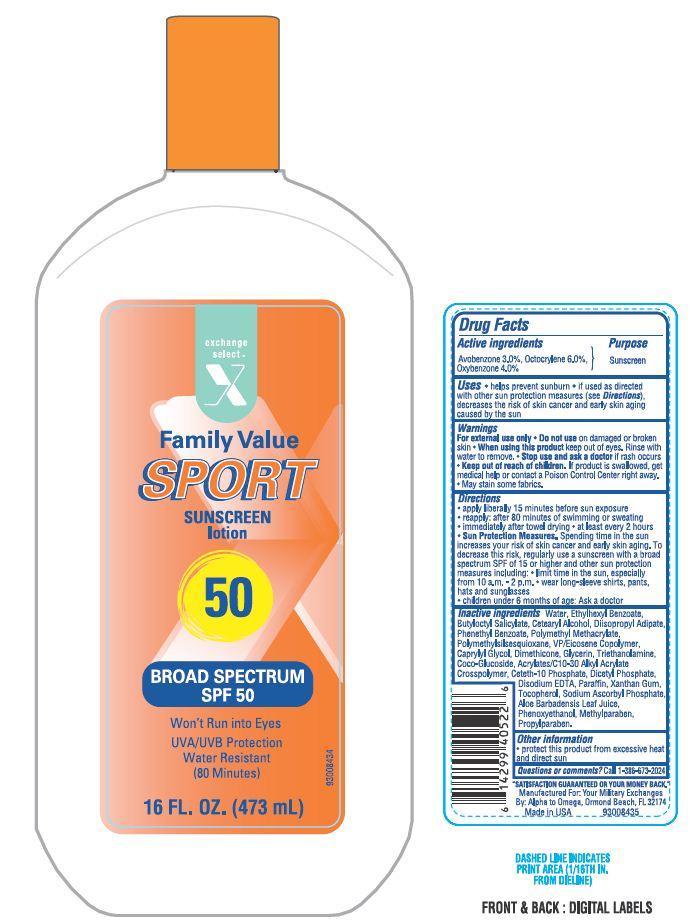 DRUG LABEL: EXCEL SPORT
NDC: 55301-020 | Form: LOTION
Manufacturer: ARMY AND AIR FORCE EXCHANGE SERVICE
Category: otc | Type: HUMAN OTC DRUG LABEL
Date: 20130806

ACTIVE INGREDIENTS: AVOBENZONE 3 g/100 g; OCTOCRYLENE 6 g/100 g; OXYBENZONE 4 g/100 g
INACTIVE INGREDIENTS: WATER; 2-ETHYLHEXYL BENZOATE; BUTYLOCTYL SALICYLATE; CETOSTEARYL ALCOHOL; DIISOPROPYL ADIPATE; PHENETHYL BENZOATE; CAPRYLYL GLYCOL; DIMETHICONE; GLYCERIN; TROLAMINE; COCO GLUCOSIDE; CETETH-10 PHOSPHATE; DIHEXADECYL PHOSPHATE; EDETATE DISODIUM; PARAFFIN; XANTHAN GUM; TOCOPHEROL; SODIUM ASCORBYL PHOSPHATE; ALOE VERA LEAF; PHENOXYETHANOL; METHYLPARABEN; PROPYLPARABEN

Drug Facts

Active ingredients

Avobenzone 3.0%

Octocrylene 6.0%

Oxybenzone 4.0%

Purpose

Sunscreen

Uses

- Helps prevent sunburn
- If used as directed with other sun protection measures (see Directions), decrease the risk of skin cancer and early skin aging caused by the sun.

Warnings

For external use only. Do not use on damaged or broken skin.

When using this product

Keep out of eyes. Rinse with water to remove.

Stop use and ask a doctor

if rash occurs

Keep out of reach of children

If swallowed, get medical help or contact a Poison Control Center right away. May stain some fabrics.

Directions

- apply liberally 15 minutes before sun exposure
- reapply
- after 80 minutes of swimming or sweating
- immediately after towel drying
- at least every 2 hours
- Sun Protection Measures: Spending time in the sun increases your risk of skin cancer and early skin aging. To decrease this risk, regularly use a sunscreen with a broad spectrum SPF of 15 or higher and other sun protection measures including:
- limit time in the sun, especially from 10 a.m. - 2 p.m.
- wear long-sleeve shirts, pants, hats and sunglasses
- children under 6 months of age: Ask a doctor

Inactive ingredients

Water, Ethylhexyl Benzoate, Butyloctyl Salicylate, Cetearyl Alcohol, Diisopropyl Adipate, Phenethyl Benzoate, Polymethyl Methacrylate, Polymethylsilsesquioxane, VP/Eicosene Copolymer, Caprylyl Glycol, Dimethicone, Glycerin, Triethanolamine, Coco-Glucoside, Acrylates/C10-30 Alkyl Acrylate Crosspolymer, Ceteth-10 Phosphate, Dicetyl Phosphate, Disodium EDTA, Paraffin, Xanthan Gum, Tocopherol, Sodium Ascorbyl Phosphate, Aloe Barbadensis Leaf Juice, Phenoxyethanol, Methylparaben, Propylparaben.

Other Information

- protect this product from excessive heat and direct sun

Principal Display Panel

exchange select

X

Family Value

SPORT SUNSCREEN

lotion

50

BROAD SPECTRUM

SPF 50

Won't Run into Eyes

UVA/UVB Protection

Water Resistant

(80 Minutes)

16 FL. OZ. (473 mL)

Questions or comments?

1-386-673-2024